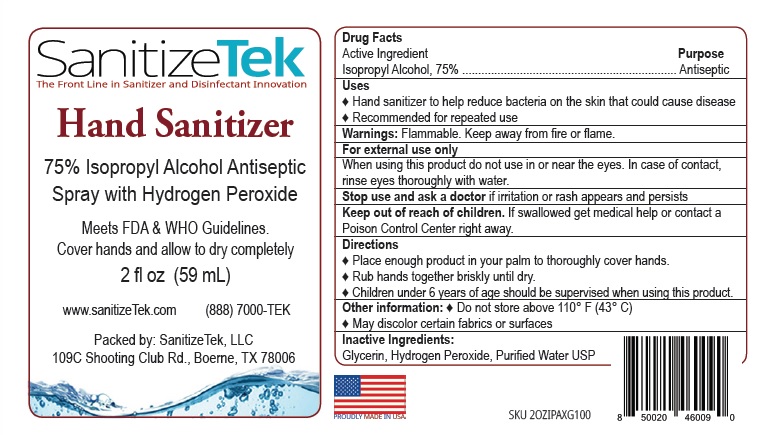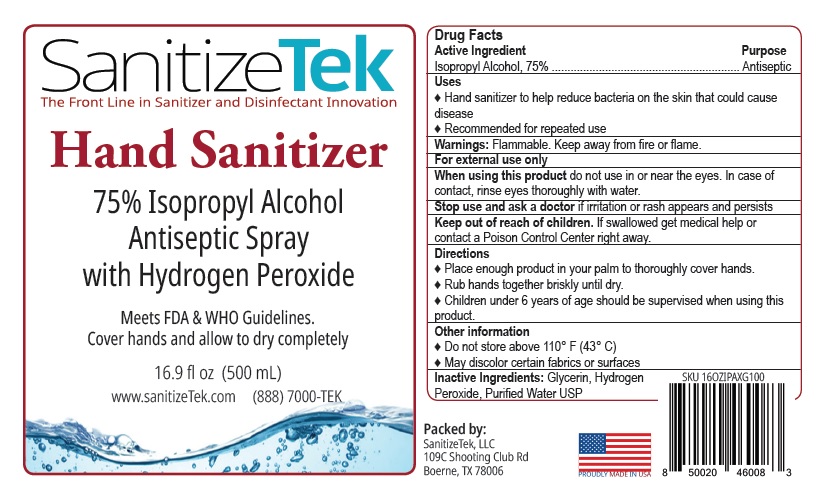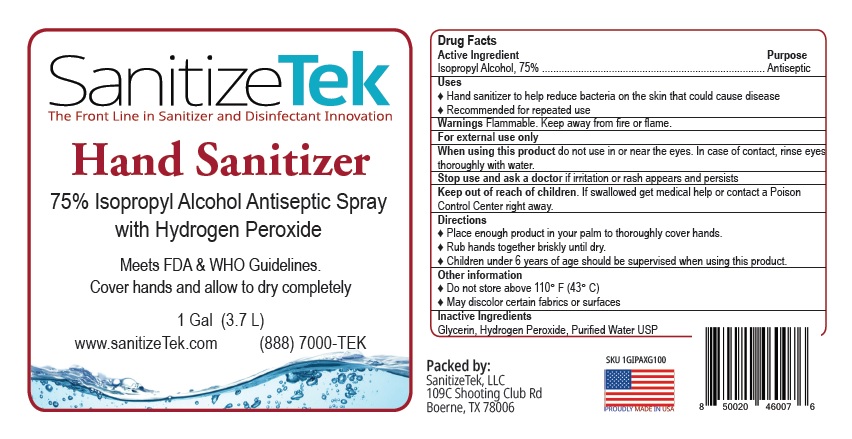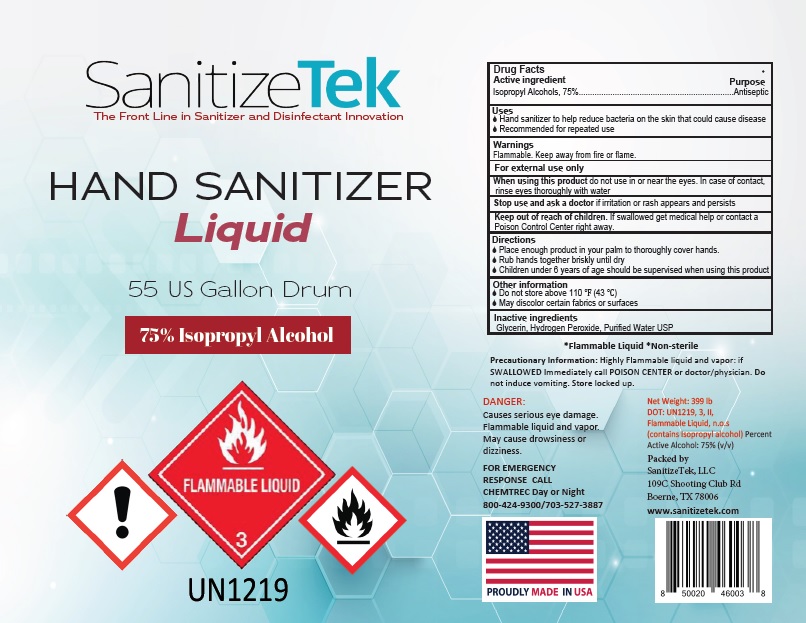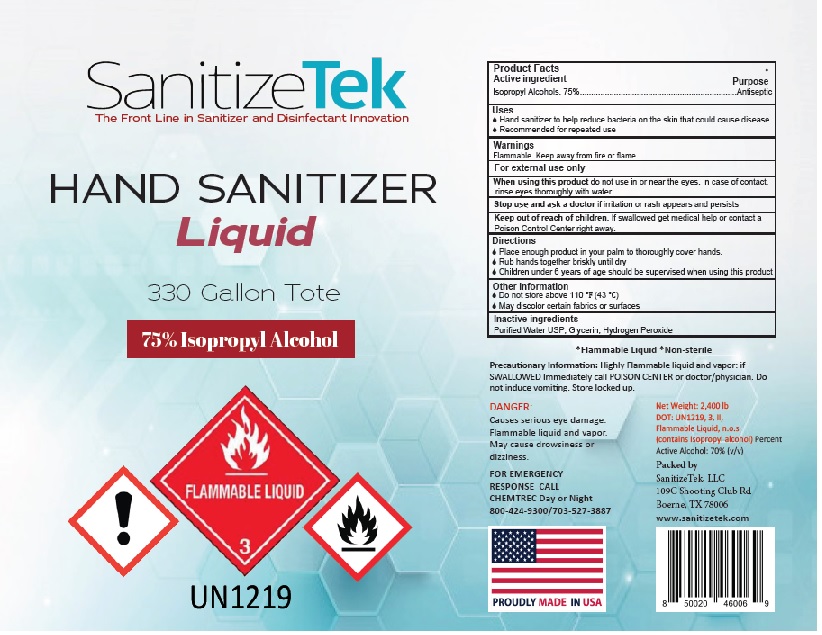 DRUG LABEL: Sanitizetek
NDC: 81737-002 | Form: LIQUID
Manufacturer: Sanitizetek, LLC
Category: otc | Type: HUMAN OTC DRUG LABEL
Date: 20210408

ACTIVE INGREDIENTS: ALCOHOL 0.750 L/1 L
INACTIVE INGREDIENTS: GLYCERIN; HYDROGEN PEROXIDE; WATER

SanitizeTek Hand Sanitizer Spray with Hydrogen Peroxide

Drug Facts

Active Ingredient
Isopropyl Alcohol, 75%

Purpose
Antiseptic

Uses
♦ Hand sanitizer to help reduce bacteria on the skin that could cause disease
♦ Recommended for repeated use

Warnings: Flammable. Keep away from fire or flame.
For external use only
When using this product do not use in or near the eyes. In case of contact, rinse eyes thoroughly with water.
Stop use and ask a doctor if irritation or rash appears and persists

Keep out of reach of children. If swallowed, get medical help or contact a Poison Control Center right away.

Directions

♦ Place enough product in your palm to thoroughly cover hands.
♦ Rub hands together briskly until dry.
♦ Children under 6 years of age should be supervised when using this product.

Other information: ♦ Do not store above 110° F (43° C)
♦ May discolor certain fabrics or surfaces

Inactive Ingredients:
Glycerin, Hydrogen Peroxide, Purified Water USP

Package Label

SanitizeTek

The Front Line in Sanitizer and Disinfectant Innovation

Hand Sanitizer

75% Isopropyl Alcohol Antiseptic

Spray with Hydrogen Peroxide

Meets FDA & WHO Guidelines.

Cover hands and allow to dry completely

2 fl oz (59 mL)

www.sanitizeTek.com (888) 7000-TEK

Packed by: SanitizeTek, LLC
109C Shooting Club Rd., Boerne, TX 78006

2 OZ

16.9 OZ

1 GAL

55 GAL

330 GAL

res